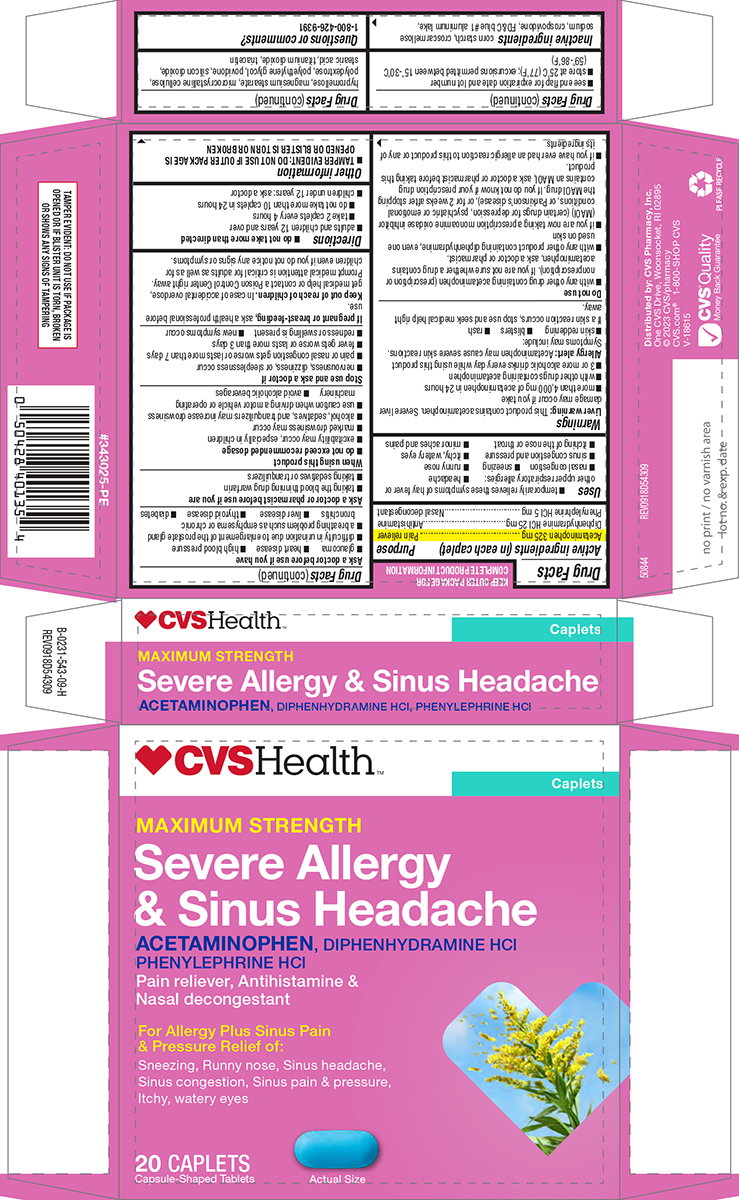 DRUG LABEL: Severe Allergy And Sinus Headache
NDC: 59779-543 | Form: TABLET, FILM COATED
Manufacturer: CVS Pharmacy
Category: otc | Type: HUMAN OTC DRUG LABEL
Date: 20260206

ACTIVE INGREDIENTS: ACETAMINOPHEN 325 mg/1 1; DIPHENHYDRAMINE HYDROCHLORIDE 25 mg/1 1; PHENYLEPHRINE HYDROCHLORIDE 5 mg/1 1
INACTIVE INGREDIENTS: STARCH, CORN; CROSCARMELLOSE SODIUM; CROSPOVIDONE, UNSPECIFIED; FD&C BLUE NO. 1 ALUMINUM LAKE; HYPROMELLOSE, UNSPECIFIED; MAGNESIUM STEARATE; MICROCRYSTALLINE CELLULOSE; POLYDEXTROSE; POLYETHYLENE GLYCOL, UNSPECIFIED; POVIDONE, UNSPECIFIED; SILICON DIOXIDE; STEARIC ACID; TITANIUM DIOXIDE; TRIACETIN

CVS 44-543-Delisted

Active ingredients (in each caplet)

Acetaminophen 325 mg
Diphenhydramine HCl 25 mg
Phenylephrine HCl 5 mg

Purpose

Pain reliever
Antihistamine
Nasal decongestant

Uses

- temporarily relieves these symptoms of hay fever or other upper respiratory allergies:
  - headache
  - nasal congestion
  - sneezing
  - runny nose
  - sinus congestion and pressure
  - itchy, watery eyes
  - itching of the nose or throat
  - minor aches and pains

Warnings

Liver warning: This product contains acetaminophen. Severe liver damage may occur if you take

- more than 4,000 mg of acetaminophen in 24 hours
- with other drugs containing acetaminophen
- 3 or more alcoholic drinks every day while using this product

Allergy alert: Acetaminophen may cause severe skin reactions. Symptoms may include:

- skin reddening
- blisters
- rash

If a skin reaction occurs, stop use and seek medical help right away.

Do not use

- with any other drug containing acetaminophen (prescription or nonprescription). If you are not sure whether a drug contains acetaminophen, ask a doctor or pharmacist.
- with any other product containing diphenhydramine, even one used on skin
- if you are now taking a prescription monoamine oxidase inhibitor (MAOI) (certain drugs for depression, psychiatric or emotional conditions, or Parkinson’s disease), or for 2 weeks after stopping the MAOI drug. If you do not know if your prescription drug contains an MAOI, ask a doctor or pharmacist before taking this product.
- if you have ever had an allergic reaction to this product or any of its ingredients

Ask a doctor before use if you have

- glaucoma
- heart disease
- high blood pressure
- difficulty in urination due to enlargement of the prostate gland
- a breathing problem such as emphysema or chronic bronchitis
- liver disease
- thyroid disease
- diabetes

Ask a doctor or pharmacist before use if you are

- taking the blood thinning drug warfarin
- taking sedatives or tranquilizers

When using this product

- do not exceed recommended dosage
- excitability may occur, especially in children
- marked drowsiness may occur
- alcohol, sedatives, and tranquilizers may increase drowsiness
- use caution when driving a motor vehicle or operating machinery
- avoid alcoholic beverages

Stop use and ask a doctor if

- nervousness, dizziness, or sleeplessness occur
- pain or nasal congestion gets worse or lasts more than 7 days
- fever gets worse or lasts more than 3 days
- redness or swelling is present
- new symptoms occur

If pregnant or breast-feeding,

ask a health professional before use.

Keep out of reach of children.

In case of accidental overdose, get medical help or contact a Poison Control Center right away. Prompt medical attention is critical for adults as well as for children even if you do not notice any signs or symptoms.

Directions

- do not take more than directed
- adults and children 12 years and over
  - take 2 caplets every 4 hours
  - do not take more than 10 caplets in 24 hours
- children under 12 years: ask a doctor

Other information

- see end flap for expiration date and lot number
- TAMPER EVIDENT: DO NOT USE IF OUTER PACKAGE IS OPENED OR BLISTER IS TORN OR BROKEN
- store at 25°C (77°F); excursions permitted between 15°-30°C (59°-86°F)

Inactive ingredients

corn starch, croscarmellose sodium, crospovidone, FD&C blue #1 aluminum lake, hypromellose, magnesium stearate, microcrystalline cellulose, polydextrose, polyethylene glycol, povidone, silicon dioxide, stearic acid, titanium dioxide, triacetin

Questions or comments?

1-800-426-9391

Principal Display Panel

♥ CVS Health™

Caplets

MAXIMUM STRENGTH
Severe Allergy
& Sinus Headache
ACETAMINOPHEN, DIPHENHYDRAMINE HCl
PHENYLEPHRINE HCl

Pain reliever, Antihistamine &
Nasal decongestant

For Allergy Plus Sinus Pain
& Pressure Relief of:
Sneezing, Runny nose, Sinus headache,
Sinus congestion, Sinus pain & pressure,
Itchy, watery eyes

20 CAPLETS
Capsule-Shaped Tablets

Actual Size

TAMPER EVIDENT: DO NOT USE IF PACKAGE IS
OPENED OR IF BLISTER UNIT IS TORN, BROKEN
OR SHOWS ANY SIGNS OF TAMPERING

Distributed by: CVS Pharmacy, Inc.
One CVS Drive, Woonsocket, RI 02895
© 2023 CVS/pharmacy
CVS.com® 1-800-SHOP CVS
V-18615

CVS®Quality
Money Back Guarantee

50844 REV0918D54309

CVS 44-543